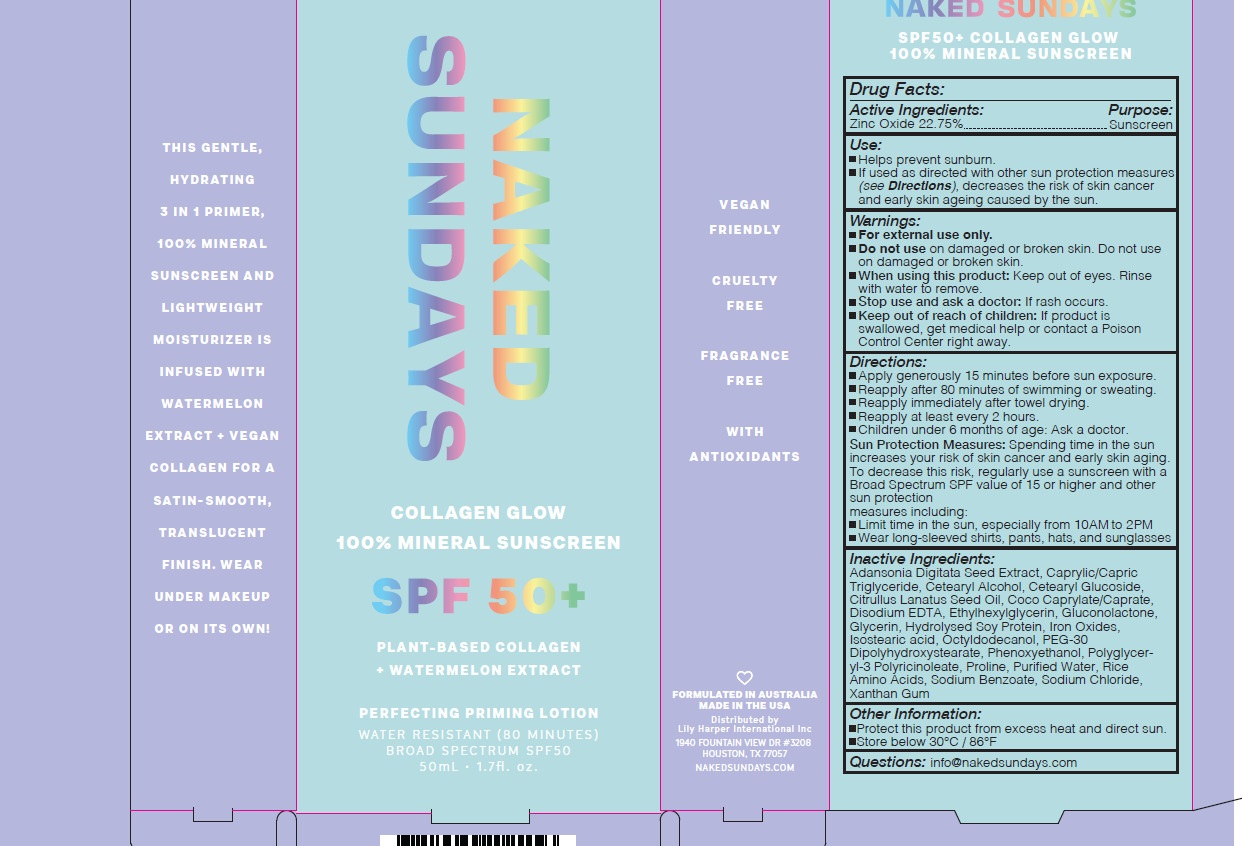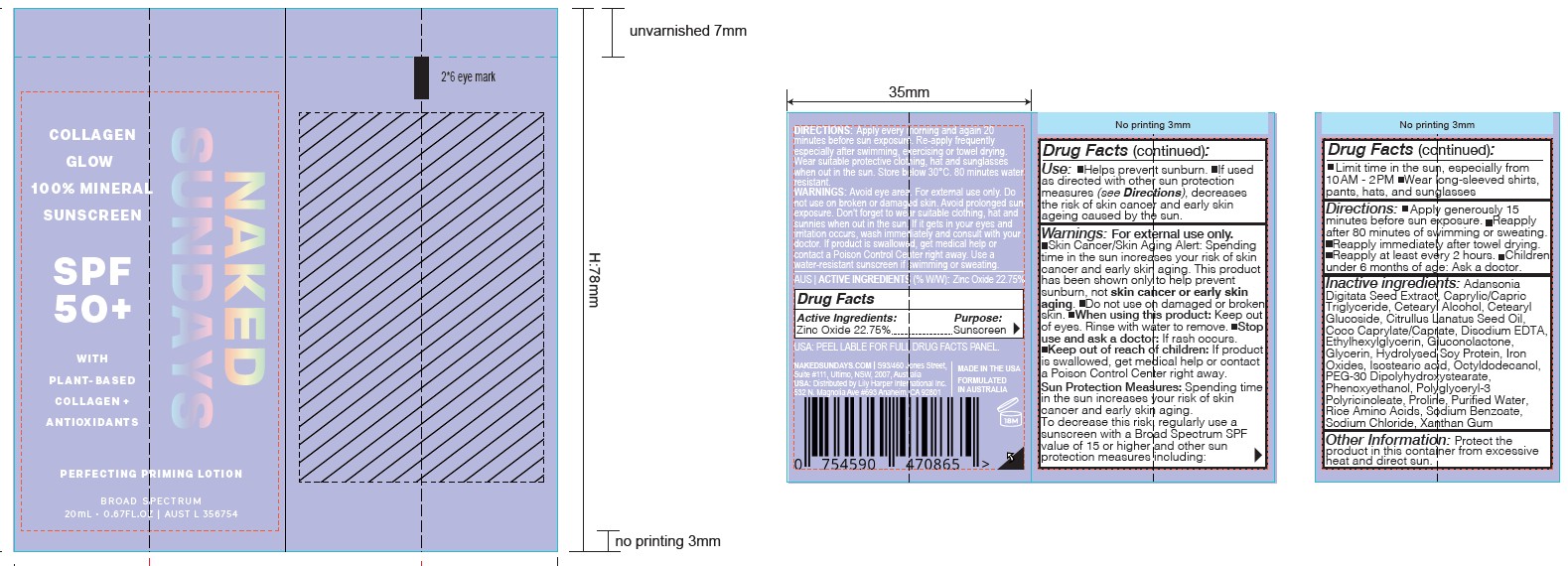 DRUG LABEL: COLLAGEN GLOW MINERAL SUNSCREEN
NDC: 81104-100 | Form: LOTION
Manufacturer: NAKED SUNDAYS PTY LTD
Category: otc | Type: HUMAN OTC DRUG LABEL
Date: 20250908

ACTIVE INGREDIENTS: ZINC OXIDE 22.75 g/100 mL
INACTIVE INGREDIENTS: CETOSTEARYL ALCOHOL; COCO-CAPRYLATE; EDETATE DISODIUM; GLUCONOLACTONE; ADANSONIA DIGITATA SEED; ORYZA SATIVA WHOLE; HYDROLYZED SOY PROTEIN (ENZYMATIC; 2000 MW); ISOSTEARIC ACID; TRICAPRIN; OCTYLDODECANOL; PEG-30 DIPOLYHYDROXYSTEARATE; POLYGLYCERYL-3 RICINOLEATE; PROLINE; WATER; SODIUM BENZOATE; SODIUM CHLORIDE; ETHYLHEXYLGLYCERIN; PHENOXYETHANOL; CETEARYL GLUCOSIDE

NAKED SUNDAYS COLLAGEN GLOW MINERAL SUNSCREEN

ACTIVE INGREDIENT

ZINC OXIDE 22.75%

Purpose

Sunscreen

USES

- Helps prevent sunburn.
- If used as directed with other sun protection measures (see directions), decreases the risk of skin cancer and early skin ageing caused by the sun.

WARNINGS

For external use only.

- Do not use on damaged or broken skin.
- When using this product: keep out of eyes. Rinse with water to remove.
- Stop use and ask a doctor if: rash occurs.

- CONTAINS SODIUM BENZOATE.

Keep out of reach of children. If product is swallowed, get medical help or contact a Poison Control Center right away.

DIRECTIONS

- APPLY GENEROUSLY 15 MINUTES BEFORE SUN EXPOSURE.
- Reapply after 80 minutes of swimming or sweating.
- Reapply immediately after towel drying.
- Reapply at least every 2 hours.
- Children under 3 years of age: Ask a doctor.

SUN PROTECTION MEASURES:

Spending time in the sun increases your risk of skin cancer and early skin aging. To decrease this risk, regularly use a sunscreen with a Broad Spectrum SPF value of 15 or higher and other sun protection measures including:

- Limit time in the sun, especially from 10.00AM - 2.00PM
- Wear long-sleeved shirts, pants, hats, and sunglasses

INACTIVE INGREDIENTS

CETOSTEARYL ALCOHOL (UNII: 2DMT128M1S) ,COCO-CAPRYLATE (UNII: 4828G836N6) ,EDETATE DISODIUM (UNII: 7FLD91C86K),GLUCONOLACTONE (UNII: WQ29KQ9POT),ADANSONIA DIGITATA SEED (UNII: 2936P60TPX), ORYZA SATIVA WHOLE (UNII: 84IVV0906Z),HYDROLYZED SOY PROTEIN (ENZYMATIC; 2000 MW) (UNII: 1394NXB9L6),ISOSTEARIC ACID (UNII: X33R8U0062),TRICAPRIN (UNII: O1PB8EU98M),OCTYLDODECANOL (UNII: 461N1O614Y),PEG-30 DIPOLYHYDROXYSTEARATE (UNII: 9713Q0S7FO),POLYGLYCERYL-3 RICINOLEATE (UNII: MZQ63P0N0W)
PROLINE (UNII: 9DLQ4CIU6V),WATER (UNII: 059QF0KO0R),SODIUM BENZOATE (UNII: OJ245FE5EU),SODIUM CHLORIDE (UNII: 451W47IQ8X),ETHYLHEXYLGLYCERIN (UNII: 147D247K3P),PHENOXYETHANOL (UNII: HIE492ZZ3T)
CETEARYL GLUCOSIDE (UNII: 09FUA47KNA)

OTHER INFORMATION

Protect the product in this container from excessive heat and direct sun.